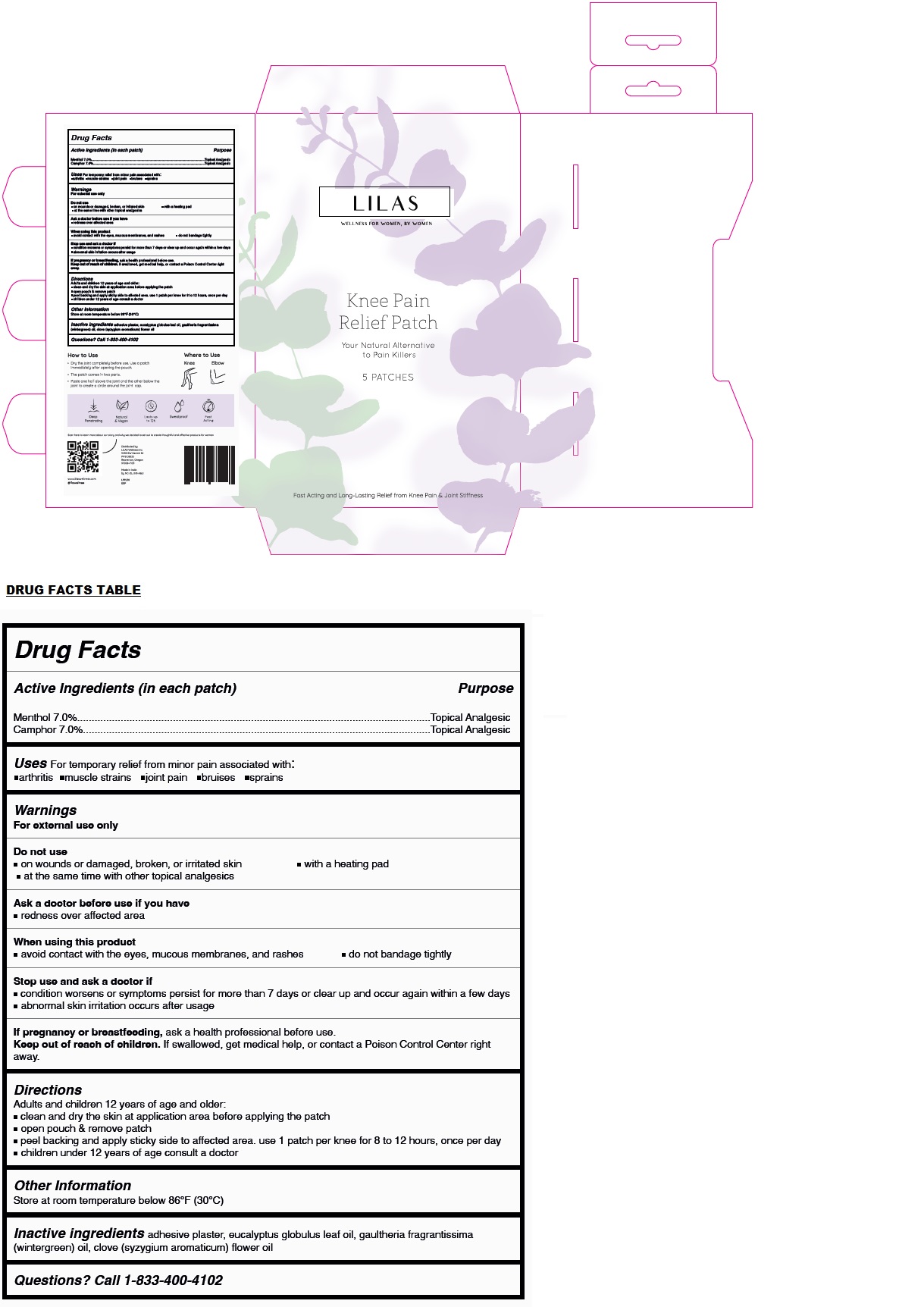 DRUG LABEL: LILAS Knee Pain Relief Patch
NDC: 72670-002 | Form: PATCH
Manufacturer: Lilas Wellness, Inc.
Category: otc | Type: HUMAN OTC DRUG LABEL
Date: 20231212

ACTIVE INGREDIENTS: MENTHOL, UNSPECIFIED FORM 308 mg/1 1; CAMPHOR (NATURAL) 308 mg/1 1
INACTIVE INGREDIENTS: EUCALYPTUS OIL; METHYL SALICYLATE; CLOVE OIL

LILAS Knee Pain Relief Patch

Active Ingredients (in each patch)

Menthol 7.0%
Camphor 7.0%

Purpose

Topical Analgesic

Uses

For temporary relief from minor pain associated with: • arthritis • muscle strains • joint pain • bruises • sprains

Warnings

For external use only

Do not use
• on wounds or damaged, broken, or irritated skin • with a heating pad
• at the same time with other topical analgesics

Ask a doctor before use if you have
• redness over affected area

When using this product
• avoid contact with the eyes, mucous membranes, and rashes • do not bandage tightly

Stop use and ask a doctor if
• condition worsens or symptoms persist for more than 7 days or clear up and occur again within a few days
• abnormal skin irritation occurs after usage

If pregnancy or breastfeeding, ask a health professional before use.

Keep out of reach of children. If swallowed, get medical help, or contact a Poison Control Center right away.

Directions

Adults and children 12 years of age and older:
• clean and dry the skin at application area before applying the patch
• open pouch & remove patch
• peel backing and apply sticky side to affected area. use 1 patch per knee for 8 to 12 hours, once per day
• children under 12 years of age consult a doctor

Other Information

Store at room temperature below 86°F (30°C)

Inactive ingredients

adhesive plaster, eucalyptus globulus leaf oil, gaultheria fragrantissima (wintergreen) oil, clove (syzgium aromaticum) flower oil

Questions?

Call 1-833-400-4102

WELLNESS FOR WOMEN, BY WOMEN

Your Natural Alternative to Pain Killers

Fast Acting and Long-Lasting Relief from Knee Pain & Joint Stiffness

How to Use

• Dry the joint completely before use. Use a patch immediately after opening the pouch.

• The patch comes in two parts.

• Paste one half above the joint and the other below the joint to create a circle around the joint cap.

Where to Use

Knee Elbow

Deep Penetrating

Natural & Vegan

Lasts up to 12h

Sweatproof

Fast Acting

Distributed by:
LILAS Wellness Inc
9450 SW Gemini Dr
PMB 38333
Beaverton, Oregon
97008-7105

Made in India
by NC-DL-378-A&U

www.lilaswellness.com

@lilaswellness